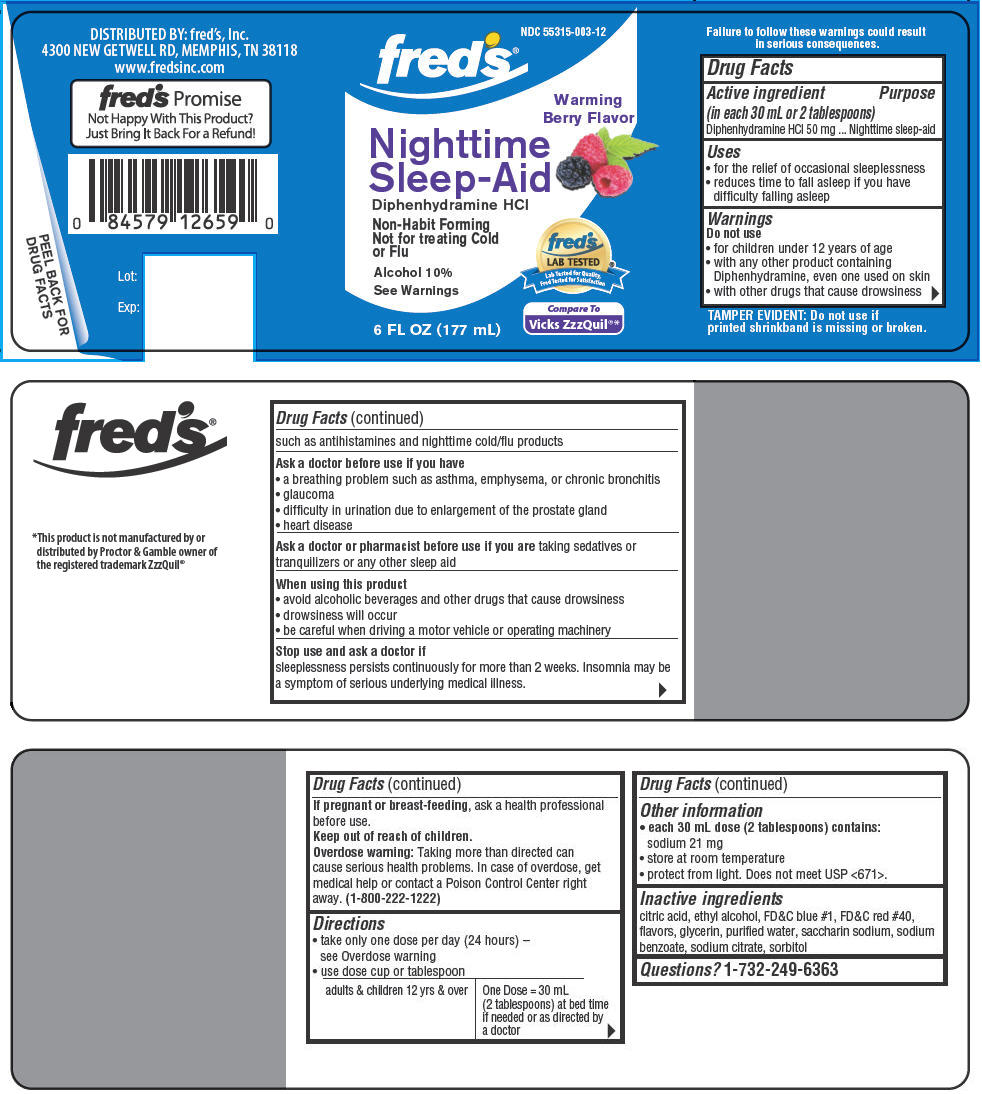 DRUG LABEL: Nighttime Sleep Aid
NDC: 55315-003 | Form: LIQUID
Manufacturer: fred's, Inc.
Category: otc | Type: HUMAN OTC DRUG LABEL
Date: 20131230

ACTIVE INGREDIENTS: Diphenhydramine Hydrochloride 50 mg/30 mL
INACTIVE INGREDIENTS: Sodium Benzoate; Citric Acid Monohydrate; Sorbitol; Saccharin Sodium; Alcohol; FD&C RED NO. 40; Sodium Citrate; Glycerin; FD&C Blue NO. 1; Water

Nighttime Sleep Aid

Drug Facts

Active ingredient (in each 30 mL or 2 tablespoons)

Diphenhydramine HCl 50 mg

Purpose

Nighttime sleep-aid

Uses

- for the relief of occasional sleeplessness
- reduces time to fall asleep if you have difficulty falling asleep

Warnings

Do not use

- for children under 12 years of age
- with any other product containing Diphenhydramine, even one used on skin
- with other drugs that cause drowsiness such as antihistamines and nighttime cold/flu products

Ask a doctor before use if you have

- a breathing problem such as asthma, emphysema, or chronic bronchitis
- glaucoma
- difficulty in urination due to enlargement of the prostate gland
- heart disease

Ask a doctor or pharmacist before use if you are taking sedatives or tranquilizers or any other sleep aid

When using this product

- avoid alcoholic beverages and other drugs that cause drowsiness
- drowsiness will occur
- be careful when driving a motor vehicle or operating machinery

Stop use and ask a doctor if

sleeplessness persists continuously for more than 2 weeks. Insomnia may be a symptom of serious underlying medical illness.

PREGNANCY OR BREAST FEEDING

If pregnant or breast-feeding, ask a health professional before use.

Keep out of reach of children.

Overdose warning

Taking more than directed can cause serious health problems. In case of overdose, get medical help or contact a Poison Control Center right away. (1-800-222-1222)

Directions

- take only one dose per day (24 hours) – see Overdose warning
- use dose cup or tablespoon

adults & children 12 yrs & over | One Dose = 30 mL (2 tablespoons) at bed time if needed or as directed by a doctor

Other information

- each 30 mL dose (2 tablespoons) contains:
  sodium 21 mg
- store at room temperature
- protect from light. Does not meet USP <671>.

Inactive ingredients

citric acid, ethyl alcohol, FD&C blue #1, FD&C red #40, flavors, glycerin, purified water, saccharin sodium, sodium benzoate, sodium citrate, sorbitol

Questions?

1-732-249-6363

DISTRIBUTED BY: fred's, Inc.
4300 NEW GETWELL RD, MEMPHIS, TN 38118

PRINCIPAL DISPLAY PANEL - 177 mL Bottle Label

NDC 55315-003-12
fred's®

Warming
Berry Flavor

Nighttime
Sleep-Aid

Diphenhydramine HCl

Non-Habit Forming
Not for treating Cold
or Flu

Alcohol 10%

See Warnings

6 FL OZ (177 mL)

fred's
LAB TESTED
Lab Tested for Quality
Fred Tested for Satisfaction

Compare To
Vicks ZzzQuil®*